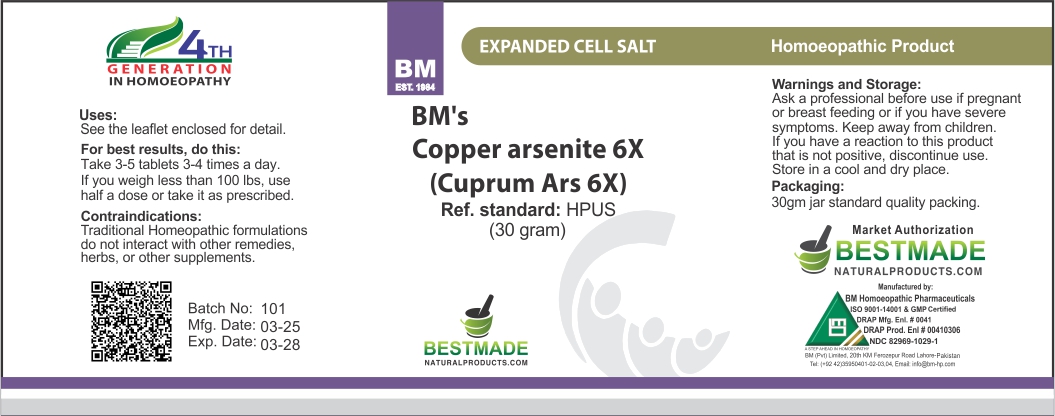 DRUG LABEL: Bestmade Natural Products Copper Arsenite (Cuprum Ars)
NDC: 82969-1029 | Form: TABLET, SOLUBLE
Manufacturer: Bestmade Natural Products
Category: homeopathic | Type: HUMAN OTC DRUG LABEL
Date: 20250526

ACTIVE INGREDIENTS: CUPRIC ARSENITE 6 [hp_X]/6 [hp_X]
INACTIVE INGREDIENTS: LACTOSE 6 [hp_X]/6 [hp_X]

Copper Arsenite 6X

DOSAGE AND ADMINISTRATION

For best results, do this:

Take 3-5 tablets 3-4 times a day.

If you weigh less than 100 lbs, use half a dose or take it as prescribed.

Contraindications:

Traditional Homeopathic formulations do not interact with other remedies, herbs, or other supplements.

Inactive:

Lactose Sugar Base to Preserve Remedy

Active Ingredients:

Copper Arsenite 6X(HPUS)

Uses:

Use the leaflet enclosed for detail.

Uses:

Use the leaflet enclosed for detail.

KEEP OUT OF REACH OF CHILDREN

Warnings and Storage:

Ask a professional before use if pregnant or breast feeding or if you have severe symptoms. Keep away from children. If you have a reaction to this product that is not positive, discontinue use.

Store in a cool and dry place.

Packaging:

30gm jar standard quality packing.

Warnings and Storage:

Ask a professional before use if pregnant or breast feeding or if you have severe symptoms. Keep away from children. If you have a reaction to this product that is not positive, discontinue use.

Store in a cool and dry place.

Packaging:

30gm jar standard quality packing.

Entire package label